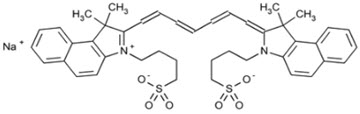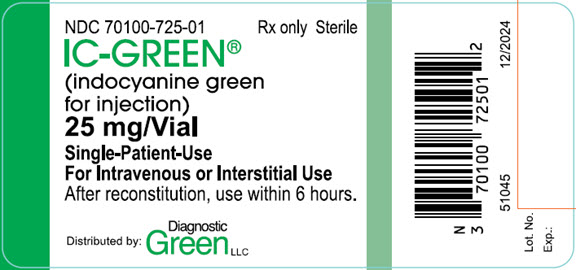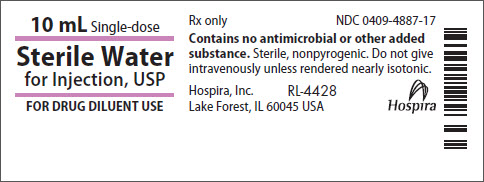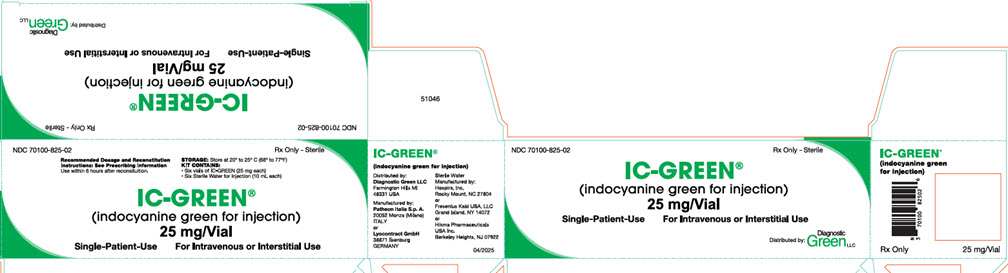 DRUG LABEL: IC-Green
NDC: 70100-825 | Form: KIT | Route: INTRAVENOUS
Manufacturer: Renew Pharmaceuticals Limited
Category: prescription | Type: HUMAN PRESCRIPTION DRUG LABEL
Date: 20250530

ACTIVE INGREDIENTS: INDOCYANINE GREEN 25 mg/1 1; WATER 1 mL/1 mL
INACTIVE INGREDIENTS: WATER; NITROGEN

HIGHLIGHTS OF PRESCRIBING INFORMATION

These highlights do not include all the information needed to use IC-GREEN safely and effectively. See full prescribing information for IC-GREEN.
IC-GREEN® (indocyanine green for injection), for intravenous or interstitial use
Initial U.S. Approval: 1959

RECENT MAJOR CHANGES

Indications and Usage, For determining Cardiac Output, Hepatic Function, and Liver Blood Flow (1.1) Removed 12/2024

Indications and Usage (1.1, 1.2, 1.3) 12/2024

Dosage and Administration, Indicator-Dilution Studies and Hepatic Function Studies (2.1, 2.2) Removed 12/2024

Dosage and Administration (2.1, 2.2, 2.3, 2.5) 12/2024

1 INDICATIONS AND USAGE

- Fluorescence imaging of vessels (micro- and macro-vasculature), blood flow and tissue perfusion before, during and after vascular, gastrointestinal, organ transplant, plastic, micro- and reconstructive surgeries, including general minimally invasive surgical procedures, in adults and pediatric patients aged 1 month and older (1.1)
- Fluorescence imaging of extrahepatic biliary ducts in adults and pediatric patients aged 12 years and older (1.2)
- Fluorescence imaging of lymph nodes and lymphatic vessels during lymphatic mapping in adults with cervical and uterine cancer (1.3)
- Ophthalmic angiography in adults and pediatric patients (1.4)

2 DOSAGE AND ADMINISTRATION

- Visualization of vessels, blood flow and tissue perfusion (2.5 mg/mL solution)
  - 1.25 mg to 5 mg by intravenous injection is recommended for a surgical procedure in adults and pediatric patients aged 1 month and older.
  - 3.75 mg to 10 mg by intravenous injection is recommended for visualization of perfusion in extremities through the skin for plastic, micro- and reconstructive surgeries in adults.
  - Additional doses may be administered. Do not exceed a total dose of 2 mg/kg. (2.1)
- Visualization of extrahepatic biliary ducts in adults and pediatric patients aged 12 years and older (2.5 mg/mL solution)
  - 2.5 mg by intravenous injection at least 45 minutes prior to surgery.
  - Additional doses may be administered. Do not exceed a total dose of 2 mg/kg. (2.2)
- Lymphatic mapping of cervical and uterine cancer in adults (1.25 mg/mL solution)
  - 5 mg interstitially as four 1 mL injections.
  - See Full Prescribing Information for injection techniques. (2.3)
- Ophthalmic Angiography
  - Doses up to 40 mg in 2 ml of Sterile Water for Injection by intravenous injection. (2.4)
- See Full Prescribing Information for reconstitution instructions. (2.5).

3 DOSAGE FORMS AND STRENGTHS

For injection: 25 mg of indocyanine green as a lyophilized, green powder for reconstitution in a single-patient-use vial (3)

4 CONTRAINDICATIONS

Hypersensitivity to indocyanine green (4)

5 WARNINGS AND PRECAUTIONS

Hypersensitivity reactions: Hypersensitivity reactions including anaphylaxis and urticaria have occurred. Always have cardiopulmonary resuscitation personnel and equipment readily available and monitor patients. (5.1)

6 ADVERSE REACTIONS

The most common adverse reactions reported are anaphylaxis and urticaria. (6)

To report SUSPECTED ADVERSE REACTIONS, contact Diagnostic Green LLC at 1-844-424-3784 or FDA at 1-800-FDA-1088 or www.fda.gov/medwatch.

7 DRUG INTERACTIONS

Interference with Thyroid Radioactive Iodine Uptake Studies: Do not perform radioactive iodine uptake studies for at least one week following the use of IC-GREEN. (7)

FULL PRESCRIBING INFORMATION

1 INDICATIONS AND USAGE

1.1 Visualization of Vessels, Blood Flow and Tissue Perfusion

IC-GREEN is indicated for fluorescence imaging of vessels (micro- and macro- vasculature), blood flow and tissue perfusion before, during and after vascular, gastrointestinal, organ transplant, plastic, micro- and reconstructive surgeries, including general minimally invasive surgical procedures in adults and pediatric patients aged 1 month and older.

1.2 Visualization of Extrahepatic Biliary Ducts

IC-GREEN is indicated for fluorescence imaging of extrahepatic biliary ducts in adults and pediatric patients aged 12 years and older.

1.3 Lymphatic Mapping of Cervical and Uterine Cancer

IC-GREEN is indicated for fluorescence imaging of lymph nodes and delineation of lymphatic vessels during lymphatic mapping in adults with cervical and uterine cancer for which this procedure is a component of intraoperative management.

1.4 Ophthalmic Angiography

IC-GREEN is indicated for use in ophthalmic angiography in adults and pediatric patients.

2 DOSAGE AND ADMINISTRATION

2.1 Recommended Dose, Administration and Imaging for Visualization of Vessels, Blood Flow and Tissue Perfusion

Dosing

Adults:

The recommended dose of IC-GREEN for a single image sequence for visualization of vessels, blood flow and tissue perfusion in adults is 1.25 mg to 5 mg administered intravenously as 0.5 mL to 2 mL of a 2.5 mg/mL solution.

For visualization of perfusion in extremities through the skin in adults, the recommended dose is 3.75 mg to 10 mg administered intravenously as 1.5 mL to 4 mL of a 2.5 mg/mL solution.

Immediately flush with a 10 mL bolus of 0.9% Sodium Chloride Injection.

Pediatric patients aged 1 month and older:

The recommended dose of IC-GREEN for a single image sequence for visualization of vessels, blood flow and tissue perfusion in pediatric patients aged 1 month and older is 1.25 mg to 5 mg administered intravenously as 0.5 mL to 2 mL of a 2.5 mg/mL solution. Lower doses may be administered in younger patients and in those with lower body weight. Adjust the amount and type of flush to avoid volume and/or sodium overload.

In both adults and pediatric patients aged 1 month and older, additional doses may be administered to obtain imaging sequences during the procedure. Do not exceed the maximum total dose of 2 mg/kg.

Administration

Prior to the imaging procedure, draw up the desired dose of IC-GREEN solution into appropriate syringes and prepare a 10 mL syringe of 0.9% Sodium Chloride Injection.

Administer via a central or peripheral venous line using a three-way stopcock attached to an injection port on the infusion line. Inject the prepared IC-GREEN into the line as a tight bolus. Immediately switch the access on the stopcock and inject the prepared flush.

Imaging Instructions

IC-GREEN may be used with an FDA-authorized imaging device that is intended to be used with indocyanine green for fluorescence imaging of vessels, blood flow and tissue perfusion.

A fluorescence response should be visible in blood vessels within 5 seconds to 15 seconds after injection.

2.2 Recommended Dose, Administration and Imaging for Visualization of Extrahepatic Biliary Ducts

Dosing and Administration

The recommended dose of IC-GREEN for visualization of extrahepatic biliary ducts in adults and pediatric patients aged 12 years and older is 2.5 mg administered intravenously as 1 mL of a 2.5 mg/mL solution at least 45 minutes prior to surgery.

Additional doses may be administered to obtain imaging sequences during the procedure.

Do not exceed a total dose of 2 mg/kg.

Imaging Instructions

IC-GREEN may be used with an FDA-authorized imaging device that is intended to be used with indocyanine green for fluorescence imaging of extrahepatic biliary ducts.

Fluorescence is visible in the biliary tree within 45 minutes after injection.

2.3 Recommended Dose, Administration and Imaging for Lymphatic Mapping of Cervical and Uterine Cancer

Dosing and Administration

The recommended dose of IC-GREEN for lymphatic mapping of cervical and uterine cancer in adults is 5 mg administered interstitially as four 1 mL injections of a 1.25 mg/mL solution into the cervix, at the 3 o’ clock and the 9 o’clock positions with a superficial (1 mm to 3 mm) and a deep (1 cm to 3 cm) injection at each position.

Imaging Instructions

IC-GREEN may be used with an FDA-authorized imaging device that is intended to be used with indocyanine green for fluorescence imaging of lymph nodes and delineation of lymphatic vessels during lymphatic mapping of cervical and uterine cancer.

Fluorescent lymphatic vessels and lymph nodes should begin to be visible within 1 minute after injection.

2.4 Recommended Dose and Administration for Ophthalmic Angiography

Dosing and Administration

Doses up to 40 mg IC-GREEN in 2 mL of Sterile Water for Injection depending on the imaging equipment and technique used should be administered intravenously and immediately followed by a 5 mL bolus of 0.9% Sodium Chloride Injection. The antecubital vein can be used for IC-GREEN administration.

2.5 Reconstitution Instructions

General

- Prepare IC-GREEN using aseptic techniques prior to procedure.
- Inspect the reconstituted solution for particulate matter. The reconstituted solution should be a clear, green solution.
- Use the prepared solution within 6 hours.
- Discard any unused product.

Visualization of Vessels, Blood Flow, Tissue Perfusion and Extrahepatic Biliary Ducts

Dissolve 25 mg of IC-GREEN with 10 mL Sterile Water for Injection to form a concentration of 2.5 mg/mL indocyanine green.

Lymphatic Mapping of Cervical and Uterine Cancer

Dissolve 25 mg of IC-GREEN with 20 mL Sterile Water for Injection to form a concentration of 1.25 mg/mL indocyanine green.

Ophthalmic Angiography

Dissolve doses up to 40 mg of IC-GREEN with 2 mL Sterile Water for Injection.

3 DOSAGE FORMS AND STRENGTHS

For injection: 25 mg of indocyanine green as a sterile, lyophilized, green powder for reconstitution provided in a 25 mL single-patient-use vial.

4 CONTRAINDICATIONS

IC-GREEN is contraindicated in patients with a history of hypersensitivity to indocyanine green. Reactions have included anaphylaxis [see Warnings and Precautions (5.1)].

5 WARNINGS AND PRECAUTIONS

5.1 Hypersensitivity Reactions

Hypersensitivity reactions including anaphylaxis, urticaria and deaths due to anaphylaxis have been reported following intravenous administration of IC-GREEN [see Adverse Reactions (6)].

IC-GREEN is contraindicated in patients with a history of hypersensitivity to indocyanine green [see Contraindications (4)]. Always have cardiopulmonary resuscitation personnel and equipment readily available and monitor all patients for hypersensitivity reactions.

5.2 Interference with Thyroid Radioactive Iodine Uptake Studies

Because IC-GREEN contains sodium iodide, the iodine-binding capacity of thyroid tissue may be reduced for at least one week following administration [see Drug Interactions (7)].

6 ADVERSE REACTIONS

The following clinically significant adverse reactions are described elsewhere in the labeling:

- Hypersensitivity Reactions [see Warnings and Precautions (5.1)].

The following adverse reactions have been identified during post-approval use of IC-GREEN. Because these reactions are reported voluntarily from a population of uncertain size, it is not always possible to reliably estimate their frequency or establish a causal relationship to drug exposure.

Immune System Disorders: Anaphylaxis, urticaria

7 DRUG INTERACTIONS

Interference with Thyroid Radioactive Iodine Uptake Studies

Because IC-GREEN contains sodium iodide, the iodine-binding capacity of thyroid tissue may be reduced for at least one week following administration. Do not perform radioactive iodine uptake studies for at least one week following administration of IC-GREEN.

8 USE IN SPECIFIC POPULATIONS

8.1 Pregnancy

Risk Summary

There are no adequate and well-controlled studies of IC-GREEN in pregnant women. Available data from a very small number of scientific literature studies with indocyanine green use in pregnant women over several decades have not reported any drug associated risks for major birth defects, miscarriage, or adverse maternal or fetal outcomes. Data from one small study in which indocyanine green was administered intravenously to pregnant women during labor suggest there is no placental transfer of the drug. Animal reproduction studies have not been conducted with indocyanine green.

All pregnancies have a background risk of birth defects, loss, or other adverse outcomes. In the U.S. general population, the estimated background risk of major birth defects and miscarriage in clinically recognized pregnancies is 2 to 4% and 15 to 20%, respectively.

8.2 Lactation

Risk Summary

Seventeen cases of indocyanine green use in lactating women have been reported in the scientific literature with no adverse events observed in the breastfed infant. However, there are no data on the presence of indocyanine green in human milk or the effects on milk production. Therefore, the developmental and health benefits of breastfeeding should be considered along with the mother's clinical need for IC-GREEN and any potential adverse effects on the breastfed infant from IC-GREEN or from the underlying maternal condition.

8.4 Pediatric Use

Use of IC-GREEN for visualization of vessels, blood flow and tissue perfusion has been established in pediatric patients aged 1 month and older. Pediatric use is supported by published data in 49 pediatric patients who received indocyanine green for assessment of blood flow and tissue perfusion in cardiovascular, vascular, and plastic, micro- and reconstructive surgical procedures, and by clinical trials in adults. No overall differences in safety or effectiveness have been observed between pediatric patients and adults. The dose range was similar to the effective dose range in adults [see Dosage and Administration (2.1)]. The use of IC-GREEN for visualization of vessels, blood flow and tissue perfusion has not been established in pediatric patients aged less than 1 month.

Use of IC-GREEN for visualization of extrahepatic biliary ducts has been established in pediatric patients aged 12 years and older. Pediatric use is supported by clinical trials in adults in addition to clinical use in pediatric patients. No overall differences in safety or effectiveness have been observed between pediatric patients and adults. The dose range was similar to the effective dose range in adults [see Dosage and Administration (2.2)]. The use of IC-GREEN for visualization of extrahepatic biliary ducts has not been established in pediatric patients aged less than 12 years.

Use of IC-GREEN for visualization of lymph nodes and lymphatic vessels during lymphatic mapping for cervical and uterine cancer have not been established in pediatric patients.

Use of IC-GREEN for ophthalmic angiography has been established in pediatric patients. Pediatric use is supported by evidence from the published literature.

8.5 Geriatric Use

Of the total number of patients in clinical studies of indocyanine green for injection for visualization of vessels, blood flow and tissue perfusion, 7% were 65 and over, while 1% were 75 and over. Of the total number of patients in clinical studies of indocyanine green for injection for visualization of lymph nodes and lymphatic vessels during lymphatic mapping of cervical and uterine cancer, 9% were 65 and over, while 2% were 75 and over. Clinical studies of indocyanine green for injection for visualization of extrahepatic biliary ducts did not include sufficient numbers of patients aged 65 and over to determine whether they respond differently from younger patients.

No overall differences in safety or effectiveness were observed between these patients and younger patients, and other reported clinical experience has not identified differences in responses between elderly and younger patients. In general, dose selection for an elderly patient should be cautious, usually starting at the low end of the dosing range, reflecting the greater frequency of decreased hepatic, renal or cardiac function, and of concomitant disease or other drug therapy.

11 DESCRIPTION

IC-GREEN (indocyanine green for injection) is an optical imaging agent for intravenous or interstitial use.

Each vial contains 25 mg of indocyanine green with not more than 5% sodium iodide as a sterile, lyophilized, green powder. IC-GREEN has a pH of 5.5-7.5 when reconstituted with Sterile Water for Injection, USP.

The chemical name for Indocyanine Green is 1 HBenz[e]indolium, 2-[7-[1,3-dihydro-1,1-dimethyl-3-(4- sulfobutyl)-2H-benz[e]indol-2-ylidene]-1,3,5-heptatrienyl]-1,1-dimethyl-3-(4-sulfobutyl)-, hydroxide, inner salt, sodium salt.

Molecular Formula: C43H47N2NaO6S2; Molecular Mass: 774.96 g/mol, with the following structural formula:

Indocyanine green has a peak spectral absorption at 805 nm in blood.

12 CLINICAL PHARMACOLOGY

12.1 Mechanism of Action

When bound to proteins in plasma or in lymph fluid, indocyanine green absorbs light in the near-infrared region with peak absorption at 805 nm and emits fluorescence (light) at a slightly longer wavelength, with peak emission at 830 nm. Fluorescence imaging devices provide external energy as near infrared light for indocyanine green to absorb, resulting in excitation of the indocyanine green, and the emitted light (fluorescence) is transferred from the field of view to an image on a monitor. These optical properties of indocyanine green are utilized in fluorescence imaging of the micro- and macro-vasculature, blood flow and tissue perfusion, the extrahepatic biliary ducts, and for lymphatic mapping of lymph nodes and lymphatic vessels.

12.2 Pharmacodynamics

There are no pharmacodynamic data.

12.3 Pharmacokinetics

Distribution

Following intravenous injection, indocyanine green binds to plasma proteins (98%) and is largely confined to the intravascular compartment. Indocyanine green undergoes no significant extrahepatic or enterohepatic circulation; simultaneous arterial and venous blood estimations have shown negligible renal, peripheral, lung or cerebro-spinal uptake of the dye. After biliary obstruction, the dye appears in the hepatic lymph, independently of the bile, suggesting that the biliary mucosa is sufficiently intact to prevent diffusion of the dye, though allowing diffusion of bilirubin.

Following interstitial injection, indocyanine green binds to proteins in lymph fluid and the interstitial space, is taken up by the lymphatic vessels, and drains to the lymph nodes.

Since excessive dye extravasation does not take place in the highly fenestrated choroidal vasculature, IC-GREEN is useful in both absorption and fluorescence infrared angiography of the choroidal vasculature when using appropriate filters and film in a fundus camera.

Elimination

Indocyanine green is taken up from the plasma almost exclusively by the hepatic parenchymal cells and is secreted entirely into the bile.

13 NONCLINICAL TOXICOLOGY

13.1 Carcinogenesis, Mutagenesis, Impairment of Fertility

No studies have been performed to evaluate the potential for carcinogenicity, mutagenicity, or impairment of fertility by indocyanine green.

14 CLINICAL STUDIES

14.1 Lymphatic Mapping of Cervical and Uterine Cancer

The effectiveness of IC-GREEN for fluorescence imaging of lymph nodes and delineation of lymphatic vessels during lymphatic mapping in adults with cervical and uterine cancer has been established based on a study of another formulation of indocyanine green for injection. Below is a description of the FILM Study (NCT 02209532).

The study was a randomized, prospective, multi-center, open-label study in patients with early stage uterine or cervical cancer and no known regional nodal or metastatic disease by standard clinical evaluation. Indocyanine green and a blue dye comparator were injected into the cervix of patients at the beginning of the operative procedure.

A total of 176 patients were randomized to receive either indocyanine green followed by blue dye or blue dye followed by indocyanine green. A total of four 1 mL injections of a 1.25 mg/ml solution of indocyanine green for a total dose of 5 mg were administered interstitially into the cervix at the 3 o'clock and 9 o'clock positions with a superficial (1 mm to 3 mm) and a deep (1 cm to 3 cm) injection at each position.

Lymphatic mapping was performed intraoperatively using a fluorescence imaging device and standard light, followed by excision of tissues identified by indocyanine green, blue dye, or the surgeon's visual and palpation examination. The resected tissues were evaluated by histopathology to confirm presence of lymph nodes. The efficacy of indocyanine green in the detection of lymphatic vessels and lymph nodes during lymphatic mapping procedures was determined by the number of histology-confirmed lymph nodes detected by indocyanine green and/or the blue dye comparator.

The mean age of the 176 patients was 63 years (range: 31 to 88 years); distribution by race and ethnicity was 79% White, 4% Black or African American, 3% Asian, 13% Hispanic/Latino and 1% other.

Table 1 shows the distribution of resected, confirmed lymph nodes detected by indocyanine green or blue dye in the modified intent-to-treat population (mlTT). Among the confirmed lymph nodes identified, 93% were identified using indocyanine green, and 43% were identified using blue dye, a difference of 50% [95% confidence interval 39% to 60%].

Table 1: Distribution of Resected, Confirmed Lymph Nodes Detected by Indocyanine Green or Blue Dye (BD)
Analysis Population | Nodes (n) | All Lymph Nodes Detected with Indocyanine Green | All Lymph Nodes Detected with BD | Lymph Nodes Detected with Indocyanine Green Only | Lymph Nodes Detected with BD Only | Lymph Nodes Detected with Neither
mlTT | 513 | (476/513) 93% | (220/513) 43% | (262/513) 51% | (6/513) 1% | (31/513) 6%

Table 2 shows the number of patients with at least one resected, confirmed lymph node and the number of patients with at least one bilateral lymph node pair detected by indocyanine green or blue dye. With indocyanine green, approximately 97% of patients had at least one resected, confirmed lymph node detected and 73% had at least one bilateral lymph node pair detected, compared with 68% and 28%, respectively, with blue dye (p-values for each analysis <0.0001).

Table 2: Distribution of Patients with at Least One Confirmed Unilateral Lymph Node/ Bilateral Pair Detected by Indocyanine Green or Blue Dye (BD)
Analysis Population | Patients (n) | Patients with All Lymph Nodes Detected with Indocyanine Green | Patients with All Lymph Nodes Detected with BD | Patients with Lymph Nodes Detected with Indocyanine Green only | Patients with Lymph Nodes Detected with BD only | Patients with Lymph Nodes Detected with Neither
mlTT Unilateral* | 172 | (167/172) 97% | (118/172) 68% | (51/172) 30% | (2/172) 1% | (3/172) 3%
mlTT Bilateral** |  | (126/172) 73% | (49/172) 28% | (79/172) 46% | (2/172) 1% | (44/172) 26%
*: patients with at least one resected confirmed lymph node detected unilaterally
**: patients with at least one resected confirmed lymph node detected bilaterally

16 HOW SUPPLIED/STORAGE AND HANDLING

How Supplied

IC-GREEN (indocyanine green for injection) is supplied as a kit (NDC 70100-825-02) containing the following:

- Six 25 mL single-patient-use vials of IC-GREEN (25 mg each) as a sterile, lyophilized green powder for reconstitution NDC 70100-725-01
- Six single-dose vials of Sterile Water for Injection (10 mL each) NDC 63323-185-10 or NDC 0409-4887-17 or NDC 0641-6147-10

Storage and Handling

Store at 20°C to 25°C (68°F to 77°F).

17 PATIENT COUNSELING INFORMATION

Hypersensitivity Reactions

Advise patients to seek medical attention for reactions following injection of IC-GREEN such as difficulty breathing, swollen tongue or throat, skin reactions including hives, itching and flushed or pale skin, low blood pressure, a weak and rapid pulse and other symptoms or signs of an anaphylactic reaction [see Warnings and Precautions (5.1)].

Manufactured by:
Patheon Italia S.p.A.
20900 Monza (MB), ITALY

or

LYOCONTRACT GmbH
38871 Ilsenburg, GERMANY

Distributed by:
Diagnostic Green LLC
Farmington Hills, Ml 48331

Sterile Water for injection, USP is manufactured by:
Fresenius Kabi USA, LLC
Grand Island, NY 14072

or

Hospira, Inc.
Rocky Mount, NC 27804

or

Hikma Pharmaceuticals USA Inc.
Berkeley Heights, NJ 07922

51047

PRINCIPAL DISPLAY PANEL - Vial

Vial Label

NDC 70100-725-01 Rx only Sterile

IC-GREEN®
(indocyanine green
for injection)

25 mg/Vial

Single-Patient-Use
For Intravenous or Interstitial Use
After reconstitution, use within 6 hours.

Distributed by: Diagnostic Green LLC

51045 12/2024

Lot No.
Exp.:

PRINCIPAL DISPLAY PANEL – Sterile Water Vial

Sterile Water Label

10 mL Single-dose

Sterile Water
for Injection, USP

FOR DRUG DILUENT USE

Rx only NDC 0409-4887-17

Contains no antimicrobial or other added
substance. Sterile, nonpyrogenic. Do not give
intravenously unless rendered nearly isotonic.

Hospira, Inc. RL-4428
Lake Forest, IL 60045 USA

PRINCIPAL DISPLAY PANEL - Carton

Carton Label

NDC 70100-825-02 Rx Only - Sterile

IC-GREEN®
(indocyanine green for injection)

25 mg/Vial

Single-Patient-Use For Intravenous or Interstitial Use

Distributed by: Diagnostic Green LLC

Back Panel

NDC 70100-825-02 Rx Only - Sterile

Recommended Dosage and Reconstitution
Instructions: See Prescribing Information
Use within 6 hours after reconsituition.

STORAGE: Store at 20° to 25° C (68° to 77°F)
KIT CONTAINS:
• Six vials of IC-GREEN (25 mg each)
• Six Sterile Water for Injection (10 mL each)

IC-GREEN®
(indocyanine green for injection)

25 mg/Vial

Single-Patient-Use For Intravenous or Interstitial Use

Side Panel

IC-GREEN®
(indocyanine green for injection)

Distributed by:
Diagnostic Green LLC
Farmington Hills MI
48331 USA

Manufactured by:
Patheon Italia S.p.A.
20052 Monza (Milano)
ITALY
or
Lyocontract GmbH
38871 Ilsenburg
GERMANY

Sterile Water
Manufactured by:
Hospira, Inc.
Rocky Mount, NC 27804
or
Fresenius Kabi USA, LLC
Grand Island, NY 14072
or
Hikma Pharmaceuticals
USA Inc.
Berkeley Heights, NJ 07922

04/2025